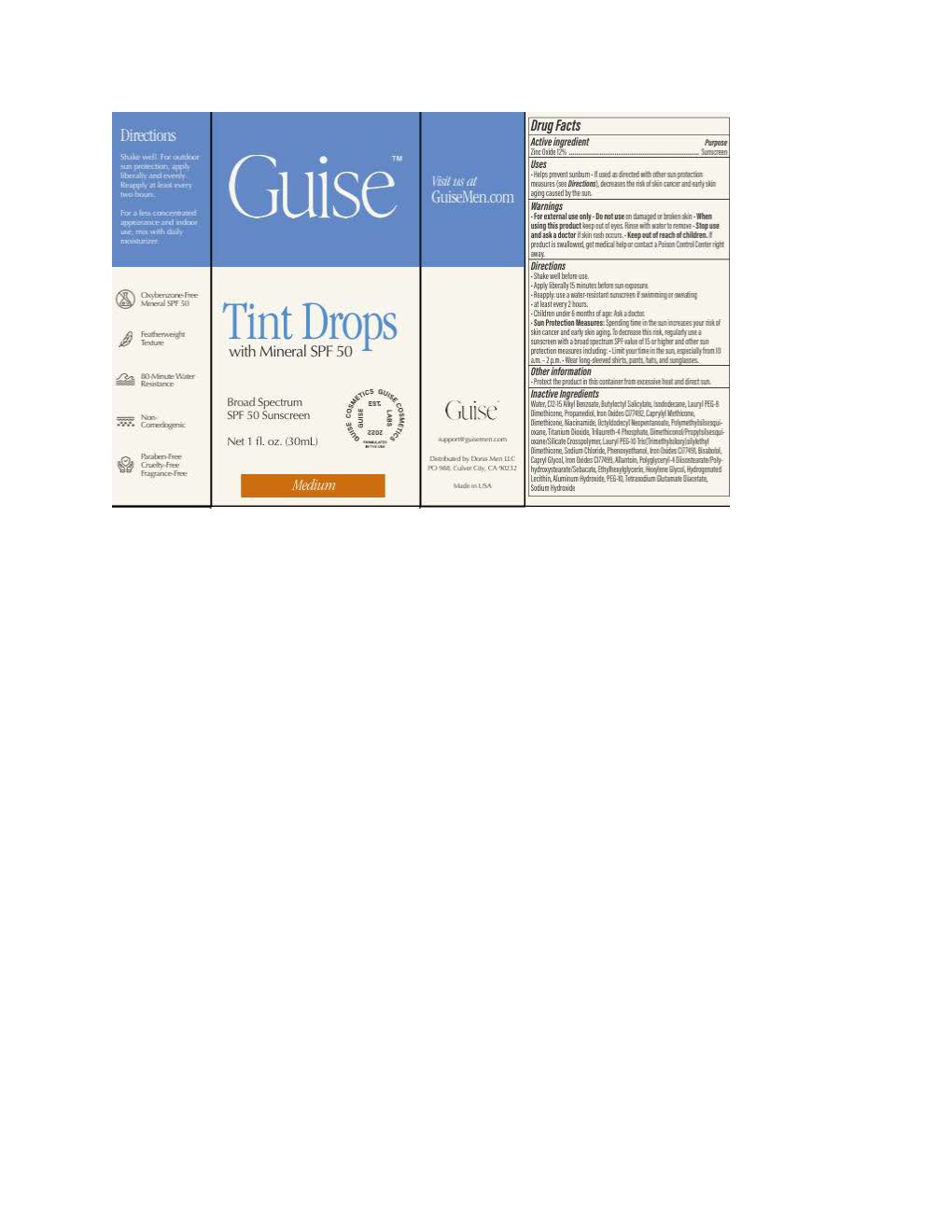 DRUG LABEL: Guise Tinted Drops
NDC: 83827-1208 | Form: LOTION
Manufacturer: Donis Men LLC
Category: otc | Type: HUMAN OTC DRUG LABEL
Date: 20250917

ACTIVE INGREDIENTS: ZINC OXIDE 132 mg/1 mL
INACTIVE INGREDIENTS: LAURYL PEG-8 DIMETHICONE (300 CPS); FERRIC OXIDE YELLOW; ALKYL (C12-15) BENZOATE; WATER; POLYMETHYLSILSESQUIOXANE (4.5 MICRONS); DIMETHICONE; NIACINAMIDE; ETHYLHEXYLGLYCERIN; HEXYLENE GLYCOL; TRILAURETH-4 PHOSPHATE; DIMETHICONOL/PROPYLSILSESQUIOXANE/SILICATE CROSSPOLYMER (450000000 MW); PROPANEDIOL; TETRASODIUM GLUTAMATE DIACETATE; FERRIC OXIDE RED; SODIUM CHLORIDE; PHENOXYETHANOL; .ALPHA.-BISABOLOL, (+)-; BUTYLOCTYL SALICYLATE; OCTYLDODECYL NEOPENTANOATE; ISODODECANE; ALLANTOIN

Guise Tinted Drops